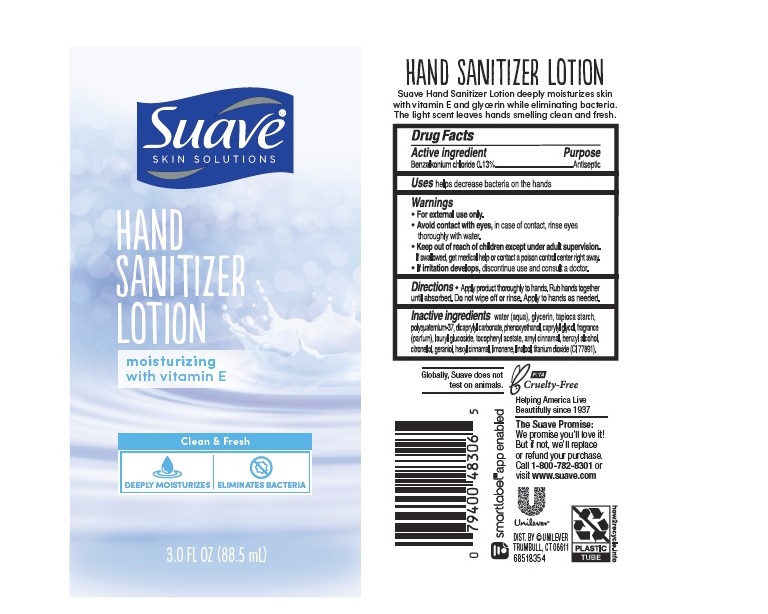 DRUG LABEL: Suave
NDC: 64942-1850 | Form: LOTION
Manufacturer: Conopco Inc. d/b/a/ Unilever
Category: otc | Type: HUMAN OTC DRUG LABEL
Date: 20221207

ACTIVE INGREDIENTS: BENZALKONIUM CHLORIDE 1.3 mg/1 mL
INACTIVE INGREDIENTS: .ALPHA.-HEXYLCINNAMALDEHYDE; .ALPHA.-AMYLCINNAMALDEHYDE; .BETA.-CITRONELLOL, (R)-; GERANIOL; STARCH, TAPIOCA; POLYQUATERNIUM-37 (10000 MPA.S); DICAPRYLYL CARBONATE; WATER; GLYCERIN; CAPRYLYL GLYCOL; LAURYL GLUCOSIDE; TITANIUM DIOXIDE; PHENOXYETHANOL; .ALPHA.-TOCOPHEROL ACETATE; LIMONENE, (+)-; LINALOOL, (+/-)-; BENZYL ALCOHOL

Suave Skin Solutions Hand Sanitizer Lotion

SUAVE SKIN SOLUTIONS HAND SANITIZER LOTION - Benzalkonium Chloride lotion

Suave Skin Solutions Hand Sanitizer Lotion

Drug Facts

Active ingredient

Benzalkonium Chloride 0.13%

Purpose

Antiseptic

Uses

helps decrease bacteria on the hands

Warnings

For external use only
Avoid contact with eyes, In case of contact, rinse eyes thoroughly with water.
If irritation develops, discontinue use and consult a doctor .

.

• Keep out of reach of children except under adult supervision.

If swallowed, get medical help or contact a poison control Center right away.

Directions

Apply product thoroughly to hands. Rub hands together until absorbed. Do not wipe off or rinse. Apply to hands as needed.

Inactive ingredients

Water (Aqua), Glycerin, Tapioca Starch, Polyquaternium-37, Dicaprylyl Carbonate, Phenoxyethanol, Caprylyl Glycol, Fragrance (Parfum), Lauryl Glucoside, Tocopheryl Acetate, Amyl Cinnamal, Benzyl Alcohol, Citronellol, Geraniol, Limonene, Linalool, Titanium Dioxide (CI 77891).

Call

1-800-782-8301 or visit www.suave.com